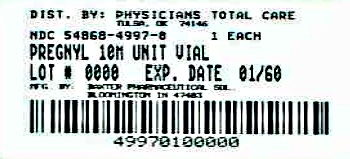 DRUG LABEL: Pregnyl
NDC: 54868-4997 | Form: KIT | Route: INTRAMUSCULAR
Manufacturer: Physicians Total Care, Inc.
Category: prescription | Type: HUMAN PRESCRIPTION DRUG LABEL
Date: 20120419

ACTIVE INGREDIENTS: CHORIOGONADOTROPIN ALFA 10000 [USP'U]/10 mL
INACTIVE INGREDIENTS: SODIUM PHOSPHATE, MONOBASIC; SODIUM PHOSPHATE, DIBASIC; SODIUM HYDROXIDE; PHOSPHORIC ACID; WATER; SODIUM CHLORIDE; BENZYL ALCOHOL

Pregnyl®
(chorionic gonadotropin for injection, USP)

DESCRIPTION

Human chorionic gonadotropin (HCG), a polypeptide hormone produced by the human placenta, is composed of an alpha and a beta sub-unit. The alpha sub-unit is essentially identical to the alpha sub-units of the human pituitary gonadotropins, luteinizing hormone (LH) and follicle-stimulating hormone (FSH), as well as to the alpha sub-unit of human thyroid-stimulating hormone (TSH). The beta sub-units of these hormones differ in amino acid sequence.

PREGNYL® (chorionic gonadotropin for injection, USP) is a highly purified pyrogen-free preparation obtained from the urine of pregnant females. It is standardized by a biological assay procedure. It is available for intramuscular injection in multiple dose vials containing 10,000 USP Units of sterile dried powder with 5 mg monobasic sodium phosphate and 4.4 mg dibasic sodium phosphate. If required, pH is adjusted with sodium hydroxide and/or phosphoric acid. Each package also contains a 10 mL vial of solvent containing: water for injection with 0.56% sodium chloride and 0.9% BENZYL ALCOHOL, WHICH IS NOT FOR USE IN NEWBORNS. If required, pH is adjusted with sodium hydroxide and/or hydrochloric acid.

CLINICAL PHARMACOLOGY

The action of HCG is virtually identical to that of pituitary LH, although HCG appears to have a small degree of FSH activity as well. It stimulates production of gonadal steroid hormones by stimulating the interstitial cells (Leydig cells) of the testis to produce androgens and the corpus luteum of the ovary to produce progesterone.

Androgen stimulation in the male leads to the development of secondary sex characteristics and may stimulate testicular descent when no anatomical impediment to descent is present. This descent is usually reversible when HCG is discontinued.

During the normal menstrual cycle, LH participates with FSH in the development and maturation of the normal ovarian follicle, and the mid-cycle LH surge triggers ovulation. HCG can substitute for LH in this function. During a normal pregnancy, HCG secreted by the placenta maintains the corpus luteum after LH secretion decreases, supporting continued secretion of estrogen and progesterone and preventing menstruation. HCG HAS NO KNOWN EFFECT ON FAT MOBILIZATION, APPETITE OR SENSE OF HUNGER, OR BODY FAT DISTRIBUTION.

INDICATIONS AND USAGE

HCG HAS NOT BEEN DEMONSTRATED TO BE EFFECTIVE ADJUNCTIVE THERAPY IN THE TREATMENT OF OBESITY. THERE IS NO SUBSTANTIAL EVIDENCE THAT IT INCREASES WEIGHT LOSS BEYOND THAT RESULTING FROM CALORIC RESTRICTION, THAT IT CAUSES A MORE ATTRACTIVE OR “NORMAL” DISTRIBUTION OF FAT, OR THAT IT DECREASES THE HUNGER AND DISCOMFORT ASSOCIATED WITH CALORIE-RESTRICTED DIETS.

1. Prepubertal cryptorchidism not due to anatomical obstruction. In general, HCG is thought to induce testicular descent in situations when descent would have occurred at puberty. HCG thus may help predict whether or not orchiopexy will be needed in the future. Although, in some cases, descent following HCG administration is permanent, in most cases, the response is temporary. Therapy is usually instituted in children between the ages of 4 and 9.
2. Selected cases of hypogonadotropic hypogonadism (hypogonadism secondary to a pituitary deficiency) in males.
3. Induction of ovulation and pregnancy in the anovulatory, infertile woman in whom the cause of anovulation is secondary and not due to primary ovarian failure, and who has been appropriately pretreated with human menotropins.

CONTRAINDICATIONS

Precocious puberty, prostatic carcinoma or other androgen-dependent neoplasm, prior allergic reaction to HCG.

WARNINGS

HCG should be used in conjunction with human menopausal gonadotropins only by physicians experienced with infertility problems who are familiar with the criteria for patient selection, contraindications, warnings, precautions, and adverse reactions described in the package insert for menotropins.

Anaphylaxis has been reported with urinary-derived HCG products.

The principal serious adverse reactions during this use are:
(1) Ovarian hyperstimulation, a syndrome of sudden ovarian enlargement, ascites with or without pain, and/or pleural effusion, (2) Rupture of ovarian cysts with resultant hemoperitoneum, (3) Multiple births, and (4) Arterial thromboembolism.

PRECAUTIONS

General

Since androgens may cause fluid retention, HCG should be used with caution in patients with cardiac or renal disease, epilepsy, migraine, or asthma.

Pediatric Use

Induction of androgen secretion by HCG may induce precocious puberty in pediatric patients treated for cryptorchidism. Therapy should be discontinued if signs of precocious puberty occur.

Geriatric Use

Clinical studies of PREGNYL® (chorionic gonadotropin for injection, USP) did not include subjects aged 65 and over.

ADVERSE REACTIONS

Headache, irritability, restlessness, depression, fatigue, edema, precocious puberty, gynecomastia, pain at the site of injection.

Hypersensitivity reactions, both localized and systemic in nature, have been reported.

DOSAGE AND ADMINISTRATION

For intramuscular use only. The dosage regimen employed in any particular case will depend upon the indication for the use, the age and weight of the patient, and the physician’s preference. The following regimens have been advocated by various authorities:

Prepubertal cryptorchidism not due to anatomical obstruction. Therapy is usually instituted in children between the ages of 4 and 9.

1. 4,000 USP Units three times weekly for three weeks.
2. 5,000 USP Units every second day for four injections.
3. 15 injections for 500 to 1,000 USP Units over a period of six weeks.
4. 500 USP Units three times weekly for four to six weeks. If this course of treatment is not successful, another series is begun one month later, giving 1,000 USP Units per injection.

Selected cases of hypogonadotropic hypogonadism in males.

1. 500 to 1,000 USP Units three times a week for three weeks, followed by the same dose twice a week for three weeks.
2. 4,000 USP Units three times weekly for six to nine months, following which the dosage may be reduced to 2,000 USP Units three times weekly for an additional three months.

Induction of ovulation and pregnancy in the anovulatory, infertile woman in whom the cause of anovulation is secondary and not due to primary ovarian failure and who has been appropriately pretreated with human menotropins.

(See prescribing information for menotropins for dosage and administration for that drug product.)

5,000 to 10,000 USP Units one day following the last dose of menotropins. (A dosage of 10,000 USP Units is recommended in the labeling for menotropins.)

Directions for Reconstitution

Two-vial package: Withdraw sterile air from lyophilized vial and inject into diluent vial. Remove 1–10 mL from diluent and add to lyophilized vial; agitate gently until powder is completely dissolved in solution.

Parenteral drug products should be inspected visually for particulate matter and discoloration prior to administration, whenever solution and container permit.

IMPORTANT: USE COMPLETELY AFTER RECONSTITUTION. RECONSTITUTED SOLUTION IS STABLE FOR 60 DAYS WHEN REFRIGERATED.

HOW SUPPLIED

Two-vial package containing:

1-10 mL lyophilized multiple dose vial containing: 10,000 USP Units chorionic gonadotropin per vial, NDC 54868-4997-0.

1-10 mL vial of solvent containing: water for injection with sodium chloride 0.56% and benzyl alcohol 0.9%,

When reconstituted, each 10 mL vial contains:

Chorionic gonadotropin | 10,000 USP Units
Monobasic sodium phosphate | 5 mg
Dibasic sodium phosphate | 4.4 mg
Sodium chloride | 0.56%
Benzyl alcohol | 0.9%

If required pH adjusted with sodium hydroxide and/or phosphoric acid.

Storage

Store at controlled room temperature 15–30°C (59–86°F). Reconstituted solution is stable for 60 days when refrigerated.

Rx Only

Manufactured for

Organon USA Inc. Roseland, NJ 07068

by Baxter Pharmaceutical Solutions LLC

Bloomington, IN 47403

©2006 Organon USA Inc.

Rev. 4/11
35039007T

Additional barcode labeling by:
Physicians Total Care, Inc.
Tulsa, Oklahoma 74146

PRINCIPAL DISPLAY PANEL - 10,000 USP Units/Vial Carton

NDC 54868-4997-0

10 mL multidose vial
with 10 mL vial of solvent

Pregnyl®
(chorionic gonadotropin
for injection, USP)

10,000
USP Units/vial

For Intramuscular
Injection Only

Rx only